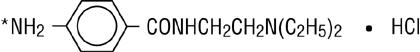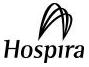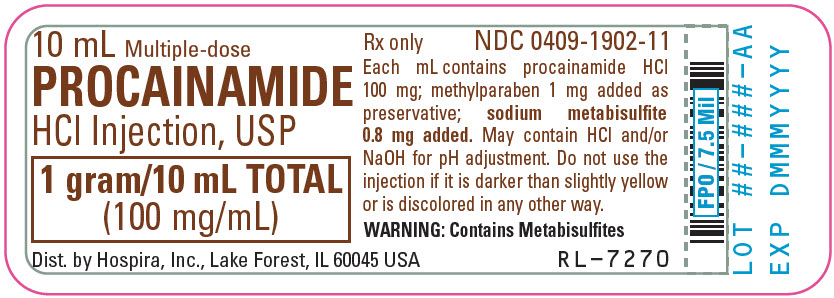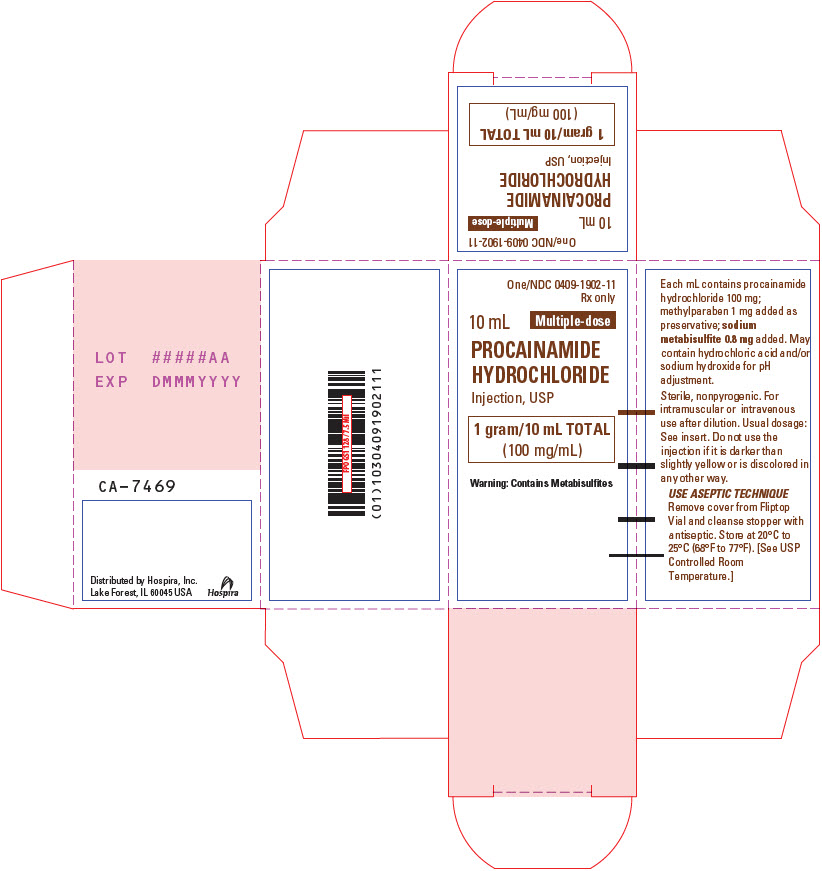 DRUG LABEL: Procainamide Hydrochloride
NDC: 0409-1902 | Form: INJECTION, SOLUTION
Manufacturer: Hospira, Inc.
Category: prescription | Type: HUMAN PRESCRIPTION DRUG LABEL
Date: 20260209

ACTIVE INGREDIENTS: PROCAINAMIDE HYDROCHLORIDE 100 mg/1 mL
INACTIVE INGREDIENTS: METHYLPARABEN 1 mg/1 mL; SODIUM METABISULFITE 0.8 mg/1 mL; WATER; HYDROCHLORIC ACID; SODIUM HYDROXIDE

PROCAINAMIDE HYDROCHLORIDE

Injection, USP

Multiple-dose Fliptop Vial Rx only

BOXED WARNING

WARNING: The prolonged administration of procainamide often leads to the development of a positive anti-nuclear antibody (ANA) test, with or without symptoms of a lupus erythematosus-like syndrome. If a positive ANA titer develops, the benefit versus risks of continued procainamide therapy should be assessed.

DESCRIPTION

Procainamide Hydrochloride Injection, USP is a sterile, nonpyrogenic solution of procainamide hydrochloride in water for injection. Each milliliter of the 10 mL vial contains procainamide hydrochloride 100 mg; methylparaben 1 mg and sodium metabisulfite 0.8 mg added in water for injection. The solution may contain hydrochloric acid and/or sodium hydroxide for pH adjustment. pH 5.0 (4.0 to 6.0). Headspace nitrogen gassed.

Procainamide Hydrochloride Injection is intended for intravenous or intramuscular administration.

Procainamide hydrochloride, a Group 1A cardiac antiarrhythmic drug, is ρ-amino-N-[2-(diethylamino) ethyl] benzamide mono-hydrochloride. It has the following structural formula:

M.W. 271.79

*(locus for acetylation to N-acetyl procainamide).

It differs from procaine which is the p-aminobenzoyl ester of 2-(diethylamino)-ethanol. Procainamide as the free base has a pKa of 9.23; the monohydrochloride is very soluble in water.

CLINICAL PHARMACOLOGY

Procainamide (PA) increases the effective refractory period of the atria, and to a lesser extent the bundle of His-Purkinje system and ventricles of the heart. It reduces impulse conduction velocity in the atria, His-Purkinje fibers, and ventricular muscle, but has variable effects on the atrioventricular (A-V) node, a direct slowing action and a weaker vagolytic effect which may speed A-V conduction slightly. Myocardial excitability is reduced in the atria, Purkinje fibers, papillary muscles, and ventricles by an increase in the threshold for excitation, combined with inhibition of ectopic pacemaker activity by retardation of the slow phase of diastolic depolarization, thus decreasing automaticity especially in ectopic sites. Contractility of the undamaged heart is usually not affected by therapeutic concentrations, although slight reduction of cardiac output may occur, and may be significant in the presence of myocardial damage. Therapeutic levels of PA may exert vagolytic effects and produce slight acceleration of heart rate, while high or toxic concentrations may prolong A-V conduction time or induce A-V block, or even cause abnormal automaticity and spontaneous firing by unknown mechanisms.

The electrocardiogram may reflect these effects by showing slight sinus tachycardia (due to the anticholinergic action) and widened QRS complexes and, less regularly, prolonged Q-T and P-R intervals (due to longer systole and slower conduction), as well as some decrease in QRS and T wave amplitude. These direct effects of PA on electrical activity, conduction, responsiveness, excitability and automaticity are characteristic of a Group 1A antiarrhythmic agent, the prototype for which is quinidine; PA effects are very similar. However, PA has weaker vagal blocking action than does quinidine, does not induce alpha-adrenergic blockade, and is less depressing to cardiac contractility.

Following intramuscular injection, procainamide is rapidly absorbed into the bloodstream, and plasma levels peak in 15 to 60 minutes, considerably faster than orally administered procainamide hydrochloride tablets or capsules which produce peak plasma levels in 90 to 120 minutes. Intravenous administration of Procainamide Hydrochloride Injection can produce therapeutic procainamide levels within minutes after infusion is started. About 15 to 20 percent of PA is reversibly bound to plasma proteins, and considerable amounts are more slowly and reversibly bound to tissues of the heart, liver, lung, and kidney. The apparent volume of distribution eventually reaches about 2 liters per kilogram body weight with a half-time of approximately five minutes. While PA has been shown in the dog to cross the blood-brain barrier, it did not concentrate in the brain at levels higher than in plasma. It is not known if PA crosses the placenta. Plasma esterases are far less active in hydrolysis of PA than of procaine. The half-time for elimination of PA is three to four hours in patients with normal renal function, but reduced creatinine clearance and advancing age each prolong the half-time of elimination of PA.

A significant fraction of the circulating PA may be metabolized in hepatocytes to N-acetylprocainamide (NAPA), ranging from 16 to 21 percent of an administered dose in "slow acetylators" to 24 to 33 percent in "fast-acetylators". Since NAPA also has significant antiarrhythmic activity and somewhat slower renal clearance than PA, both hepatic acetylation rate capability and renal function, as well as age, have significant effects on the effective biologic half-time of therapeutic action of administered PA and the NAPA derivative. Trace amounts may be excreted in the urine as free and conjugated ρ-aminobenzoic acid, 30 to 60 percent as unchanged PA, and 6 to 52 percent as the NAPA derivative. Both PA and NAPA are eliminated by active tubular secretion as well as by glomerular filtration. Action of PA on the central nervous system is not prominent, but high plasma concentrations may cause tremors. While therapeutic plasma levels for PA have been reported to be 3 to 10 mcg/mL certain patients such as those with sustained ventricular tachycardia, may need higher levels for adequate control. This may justify the increased risk of toxicity (see OVERDOSAGE). Where programmed ventricular stimulation has been used to evaluate efficacy of PA in preventing recurrent ventricular tachyarrhythmias, higher plasma levels (mean, 13.6 mcg/mL) of PA were found necessary for adequate control.

INDICATIONS AND USAGE

Procainamide hydrochloride injection is indicated for the treatment of documented ventricular arrhythmias, such as sustained ventricular tachycardia, that, in the judgement of the physician, are life-threatening. Because of the proarrhythmic effects of procainamide, its use with lesser arrhythmias is generally not recommended. Treatment of patients with asymptomatic ventricular premature contractions should be avoided.

Initiation of procainamide treatment, as with other antiarrhythmic agents used to treat life-threatening arrhythmias, should be carried out in the hospital.

Antiarrhythmic drugs have not been shown to enhance survival in patients with ventricular arrhythmias.

Because procainamide has the potential to produce serious hematological disorders (0.5 percent) particularly leukopenia or agranulocytosis (sometimes fatal), its use should be reserved for patients in whom, in the opinion of the physician, the benefits of treatment clearly outweigh the risks. (see WARNINGS and Boxed Warning.)

CONTRAINDICATIONS

Complete Heart Block: Procainamide should not be administered to patients with complete heart block because of its effects in suppressing nodal or ventricular pacemakers and the hazard of asystole. It may be difficult to recognize complete heart block in patients with ventricular tachycardia, but if significant slowing of ventricular rate occurs during PA treatment without evidence of A-V conduction appearing, PA should be stopped. In cases of second degree A-V block or various types of hemiblock, PA should be avoided or discontinued because of the possibility of increased severity of block, unless the ventricular rate is controlled by an electrical pacemaker.

Idiosyncratic Hypersensitivity: In patients sensitive to procaine or other ester-type local anesthetics, cross sensitivity to PA is unlikely. However, it should be borne in mind, and PA should not be used if it produces acute allergic dermatitis, asthma, or anaphylactic symptoms.

Lupus Erythematosus: An established diagnosis of systemic lupus erythematosus is a contraindication to PA therapy, since aggravation of symptoms is highly likely.

Torsades de Pointes: In the unusual ventricular arrhythmia called "les torsades de pointes" (twistings of the points), characterized by alternation of one or more ventricular premature beats in the directions of the QRS complexes on ECG in persons with prolonged Q-T and often enhanced U waves, Group 1A antiarrhythmic drugs are contraindicated. Administration of PA in such cases may aggravate this special type of ventricular extrasystole or tachycardia instead of suppressing it.

WARNINGS

BOXED WARNING

Mortality:

In the National Heart, Lung and Blood Institute's Cardiac Arrhythmia Suppression Trial (CAST), a long-term, multicentered, randomized, double-blind study in patients with asymptomatic non-life-threatening ventricular arrhythmias who had a myocardial infarction more than six days but less than two years previously, an excessive mortality or non-fatal cardiac arrest rate (7.7%) was seen in patients treated with encainide or flecainide compared with that seen in patients assigned to matched placebo-treated group (3.0%). The average duration of treatment with encainide or flecainide in this study was ten months.

The applicability of the CAST results to other populations (e.g., those without recent myocardial infarctions) is uncertain. Considering the known proarrhythmic properties of procainamide and the lack of evidence of improved survival for any antiarrhythmic drug in patients without life-threatening arrhythmias, the use of procainamide as well as other antiarrhythmic agents should be reserved for patients with life-threatening ventricular arrhythmias.

Blood Dyscrasias: Agranulocytosis, bone marrow depression, neutropenia, hypoplastic anemia and thrombocytopenia in patients receiving procainamide hydrochloride have been reported at a rate of approximately 0.5%. Most of these patients received procainamide within the recommended dosage range. Fatalities have occurred (with approximately 20–25 percent mortality in reported cases of agranulocytosis). Since most of these events have been noted during the first 12 weeks of therapy, it is recommended that complete blood counts including white cell, differential and platelet counts be performed at weekly intervals for the first three months of therapy, and periodically thereafter. Complete blood counts should be performed promptly if the patient develops any signs of infection (such as fever, chills, sore throat or stomatitis), bruising or bleeding. If any of these hematologic disorders are identified, procainamide therapy should be discontinued. Blood counts usually return to normal within one month of discontinuation. Caution should be used in patients with pre-existing marrow failure or cytopenia of any type. (See ADVERSE REACTIONS).

Digitalis Intoxication

Caution should be exercised in the use of procainamide in arrhythmias associated with digitalis intoxication. Procainamide can suppress digitalis-induced arrhythmias; however, if there is concomitant marked disturbance of atrioventricular conduction, additional depression of conduction and ventricular asystole or fibrillation may result. Therefore, use of procainamide should be considered only if discontinuation of digitalis, and therapy with potassium, lidocaine, or phenytoin are ineffective.

First Degree Heart Block

Caution should be exercised also if the patient exhibits or develops first degree heart block while taking PA, and dosage reduction is advised in such cases. If the block persists despite dosage reduction, continuation of PA administration must be evaluated on the basis of current benefit versus risk of increased heart block.

Predigitalization for Atrial Flutter or Fibrillation

Patients with atrial flutter or fibrillation should be cardioverted or digitalized prior to PA administration to avoid enhancement of A-V conduction which may result in ventricular rate acceleration beyond tolerable limits. Adequate digitalization reduces but does not eliminate the possibility of sudden increase in ventricular rate as the atrial rate is slowed by PA in these arrhythmias.

Congestive Heart Failure

For patients in congestive heart failure, and those with acute ischemic heart disease or cardiomyopathy, caution should be used in PA therapy, since even slight depression of myocardial contractility may further reduce cardiac output of the damaged heart.

Concurrent Other Antiarrhythmic Agents

Concurrent use of PA with other Group 1A antiarrhythmic agents such as quinidine or disopyramide may produce enhanced prolongation of conduction or depression of contractility and hypotension, especially in patients with cardiac decompensation. Such use should be reserved for patients with serious arrhythmias unresponsive to a single drug and employed only if close observation is possible.

Renal Insufficiency

Renal insufficiency may lead to accumulation of high plasma levels from conventional doses of PA, with effects similar to those of overdosage (see OVERDOSAGE), unless dosage is adjusted for the individual patient.

Myasthenia Gravis

Patients with myasthenia gravis may show worsening of symptoms from PA due to its procaine-like effect on diminishing acetylcholine release at skeletal muscle motor nerve endings, so that PA administration may be hazardous without optimal adjustment of anticholinesterase medications and other precautions.

Sulfite Sensitivity

Procainamide Hydrochloride Injection contains sodium metabisulfite, a sulfite that may cause allergic-type reactions including anaphylactic symptoms and life-threatening or less severe asthmatic episodes in certain susceptible people. The overall prevalence of sulfite sensitivity in the general population is unknown and probably low. Sulfite sensitivity is seen more frequently in asthmatic than in nonasthmatic people.

PRECAUTIONS

Blood-Pressure and ECG Monitoring

Blood pressure should be monitored with the patient supine during parenteral, especially intravenous, administration of PA (see DOSAGE AND ADMINISTRATION). There is a possibility that relatively high although transient plasma levels of PA may be attained and cause hypotension before the PA can be distributed from the plasma volume to its full apparent volume of distribution which is approximately 50 times greater. Therefore, caution should be exercised to avoid overly rapid administration of PA. If the blood pressure falls 15 mm Hg or more, PA administration should be temporarily discontinued. Electrocardiographic (ECG) monitoring is advisable as well, both for observation of the progress and response of the arrhythmia under treatment, and for early detection of any tendency to excessive widening of the QRS complex, prolongation of the P-R interval, or any signs of heart block (see OVERDOSAGE). Parenteral therapy with PA should be limited to use in hospitals in which monitoring and intensive supportive care are available, or to emergency situations in which equivalent observation and treatment can be provided.

General

Immediately after initiation of PA therapy, patients should be closely observed for possible hypersensitivity reactions. In conversion of atrial fibrillation to normal sinus rhythm by any means, dislodgement of mural thrombi may lead to embolization, which should be kept in mind.

After achieving and maintaining therapeutic plasma concentrations and satisfactory electrocardiographic and clinical responses, continued frequent periodic monitoring of vital signs and electrocardiograms is advised. If evidence of QRS widening of more than 25 percent or marked prolongation of the Q-T interval occurs, concern for overdosage is appropriate, and interruption of the PA infusion is advisable if a 50 percent increase occurs. Elevated serum creatinine or urea nitrogen, reduced creatinine clearance or history of renal insufficiency, as well as use in older patients (over age 50), provide grounds to anticipate that less than the usual dosage or infusion rate may suffice, since the urinary elimination of PA and NAPA may be reduced, leading to gradual accumulation beyond normally-predicted amounts. If facilities are available for measurement of plasma PA and NAPA, or acetylation capability, individual dose adjustment for optimal therapeutic levels may be easier, but close observation of clinical effectiveness is the most important criterion.

Information for Patients

The patient should be encouraged to disclose any past history of drug sensitivity, especially to procaine or other local anesthetic agents, or aspirin, and to report any history of kidney disease, congestive heart failure, myasthenia gravis, liver disease, or lupus erythematosus.

The patient should be counseled to report any symptoms of arthralgia, myalgia, fever, chills, skin rash, easy bruising, sore throat or sore mouth, infections, dark urine or icterus, wheezing, muscular weakness, chest or abdominal pain, palpitations, nausea, vomiting, anorexia, diarrhea, hallucinations, dizziness, or depression.

Laboratory Tests

Laboratory tests such as complete blood count (CBC), electrocardiogram and serum creatinine or urea nitrogen may be indicated depending on the clinical situation, and periodic rechecking of the CBC and ANA may be helpful in early detection of untoward reactions.

Drug Interactions

If other antiarrhythmic drugs are being used, additive effects on the heart may occur with PA administration, and dosage reduction may be necessary (see WARNINGS).

Anticholinergic drugs administered concurrently with PA may produce additive antivagal effects on A-V nodal conduction, although this is not as well documented for PA as for quinidine.

Patients taking PA who require neuromuscular blocking agents such as succinylcholine may require less than usual doses of the latter, due to PA effects on reducing acetylcholine release.

Drug/Laboratory Test Interactions

Suprapharmacologic concentrations of lidocaine and meprobamate may inhibit fluorescence of PA and NAPA, and propranolol shows a native fluorescence close to the PA/NAPA peak wavelengths, so that tests which depend on fluorescence measurement may be affected.

Carcinogenesis, Mutagenesis, Impairment of Fertility

Long-term studies in animals have not been performed.

Teratogenic Effects

Animal reproduction studies have not been conducted with PA. It also is not known whether PA can cause fetal harm when administered to a pregnant woman or can affect reproduction capacity. PA should be given to a pregnant woman only if clearly needed.

Nursing Mothers

Both PA and NAPA are excreted in human milk, absorbed by the nursing infant. Because of the potential for serious adverse reactions in nursing infants, a decision to discontinue nursing or the drug should be made, taking into account the importance of the drug to the mother.

Pediatric Use

Safety and effectiveness in pediatric patients have not been established.

ADVERSE REACTIONS

Cardiovascular System: Hypotension and serious disturbances of cardiorhythm such as ventricular asystole or fibrillation are more common with intravenous administration of PA than with intramuscular administration. Because PA is a peripheral vasodilator in concentrations higher than the usual therapeutic range, transient high plasma levels which may occur especially during intravenous administration may produce temporary but at times severe lowering of blood pressure (see OVERDOSAGE and PRECAUTIONS).

Multisystem: A lupus erythematosus-like syndrome of arthralgia, pleural or abdominal pain, and sometimes arthritis, pleural effusion, pericarditis, fever, chills, myalgia, and possibly related hematologic or skin lesions (see below) is fairly common after prolonged PA administration, perhaps more often in patients who are slow acetylators (See Boxed Warning and PRECAUTIONS). While some series have reported less than 1 in 500, others have reported the syndrome in up to 30 percent of patients on long term oral PA therapy. If discontinuation of PA does not reverse the lupoid symptoms, corticosteroid treatment may be effective.

Hematologic: Neutropenia, thrombocytopenia, or hemolytic anemia may rarely be encountered. Agranulocytosis has occurred after repeated use of PA, and deaths have been reported. (See Boxed Warning, WARNINGS section.)

Skin: Angioneurotic edema, urticaria, pruritus, flushing, and maculopapular rash have also occurred.

Gastrointestinal System: Anorexia, nausea, vomiting, abdominal pain, diarrhea or bitter taste may occur in 3 to 4 percent of patients taking oral procainamide.

Nervous System: Dizziness or giddiness, weakness, mental depression and psychosis with hallucinations have been reported.

Elevated Liver Enzymes: Elevations of transaminase with and without elevations of alkaline phosphatase and bilirubin have been reported. Some patients have had clinical symptoms (e.g., malaise, right upper quadrant pain). Deaths from liver failure have been reported.

OVERDOSAGE

Progressive widening of the QRS complex, prolonged Q-T and P-R intervals, lowering of the R and T waves, as well as increasing A-V block, may be seen with doses which are excessive for a given patient. Increased ventricular extrasystoles, or even ventricular tachycardia or fibrillation may occur. After intravenous administration but seldom after oral therapy, transient high plasma levels of PA may induce hypotension, affecting systolic more than diastolic pressures, especially in hypertensive patients. Such high levels may also produce central nervous depression, tremor, and even respiratory depression.

Plasma levels above 10 mcg/mL are increasingly associated with toxic findings, which are seen occasionally in the 10 to 12 mcg/mL range, more often in the 12 to 15 mcg/mL range, and commonly in patients with plasma levels greater than 15 mcg/mL.

Treatment of overdosage or toxic manifestations includes general supportive measures, close observation, monitoring of vital signs and possibly intravenous pressor agents and mechanical cardiorespiratory support. If available, PA and NAPA plasma levels may be helpful in assessing the potential degree of toxicity and response to therapy. Both PA and NAPA are removed from the circulation by hemodialysis but not peritoneal dialysis. No specific antidote for PA is known.

DOSAGE AND ADMINISTRATION

Procainamide Hydrochloride Injection is useful for arrhythmias which require immediate suppression and for maintenance of arrhythmia control. Intravenous therapy allows most rapid control of serious arrhythmias, including those following myocardial infarction; it should be carried out in circumstances where close observation and monitoring of the patient are possible, such as in hospital or emergency facilities. Intramuscular administration is less apt to produce temporary high plasma levels but therapeutic plasma levels are not obtained as rapidly as with intravenous administration. Oral procainamide dosage forms are preferable for less urgent arrhythmias as well as for long-term maintenance after initial parenteral PA therapy.

Intramuscular administration may be used as an alternative to the oral route for patients with less threatening arrhythmias but who are nauseated or vomiting, who are ordered to receive nothing by mouth preoperatively, or who may have malabsorptive problems. An initial daily dose of 50 mg per kg body weight may be estimated. This amount should be divided into fractional doses of one-eighth to one-quarter to be injected intramuscularly every three to six hours until oral therapy is possible. If more than three injections are given, the physician may wish to assess patient factors such as age and renal function (see below), clinical response and, if available, blood levels of PA and NAPA in adjusting further doses for that individual. For treatment of arrhythmias associated with anesthesia or surgical operation, the suggested dose is 100 to 500 mg by intramuscular injection.

Intravenous administration of Procainamide Hydrochloride Injection should be done cautiously to avoid a possible hypotensive response (see PRECAUTIONS and OVERDOSAGE). Initial arrhythmia control, under ECG monitoring, may usually be accomplished safely within a half-hour by either of the two methods which follows:

a) Direct injection into a vein or into tubing of an established infusion line should be done slowly at a rate not to exceed 50 mg per minute. It is advisable to dilute the 100 mg/mL concentration of procainamide hydrochloride prior to intravenous injection to facilitate control of dosage rate. Doses of 100 mg may be administered every 5 minutes at this rate until the arrhythmia is suppressed or until 500 mg has been administered, after which it is advisable to wait 10 minutes or longer to allow for more distribution into tissues before resuming.

b) Alternatively, a loading infusion containing 20 mg of Procainamide Hydrochloride per mL (1 g diluted to 50 mL with 5% Dextrose Injection, USP) may be administered at a constant rate of 1 mL per minute for 25 to 30 minutes to deliver 500 to 600 mg of PA. Some effects may be seen after infusion of the first 100 or 200 mg; it is unusual to require more than 600 mg to achieve satisfactory antiarrhythmic effects.

The maximum advisable dosage to be given either by repeated bolus injections or such loading infusion is 1 g.

To maintain therapeutic levels, a more dilute intravenous infusion at a concentration of 2 mg/mL is convenient (1000 mg procainamide HCl in 500 mL of 5% Dextrose Injection, USP), and may be administered at 1 to 3 mL/minute. If daily total fluid intake must be limited, a 4 mg/mL concentration (1 g of Procainamide Hydrochloride Injection in 250 mL of 5% Dextrose Injection, USP) administered at 0.5 to 1.5 mL/minute will deliver an equivalent 2 to 6 mg per minute. The amount needed in a given patient to maintain the therapeutic level should be assessed principally from the clinical response, and will depend upon the patient's weight and age, renal elimination, hepatic acetylation rate, and cardiac status, but should be adjusted for each patient based upon close observation. A maintenance infusion rate of 50 mcg/min/kg body weight to a person with a normal renal PA elimination half-time of three hours may be expected to produce a plasma level of approximately 6.5 mcg/mL.

Since the principal route for elimination of PA and NAPA is renal excretion, reduced excretion will prolong the half-life of elimination and lower the dose rate needed to maintain therapeutic levels. Advancing age reduces the renal excretion of PA and NAPA independently of reductions in creatinine clearance; compared to normal young adults, there is approximately 25 percent reduction at age 50 and 50 percent at age 75.

Intravenous therapy should be terminated if persistent conduction disturbances or hypotension develop. As soon as the patient's basic cardiac rhythm appears to be stabilized, oral antiarrhythmic maintenance therapy is preferable, if indicated and possible. A period of about three to four hours (one half-time for renal elimination, ordinarily) should elapse after the last intravenous dose before administering the first dose of Procainamide Hydrochloride tablets or capsules.

DILUTIONS AND RATES FOR INTRAVENOUS INFUSIONS*
Procainamide Hydrochloride Injection, USP

Final Concentration

Infusion
Volume†

Procainamide
Hydrochloride To Be Added

Infusion
Rate

Initial Loading Infusion

20 mg/mL

50 mL

1000 mg

1 mL/min
(for up to 25–30 min*)

Maintenance Infusion

2 mg/mL

or

4 mg/mL

500 mL

250 mL

1000 mg

1000 mg

1 to 3 mL/min

0.5 to 1.5 mL/min

The maintenance infusion rates are calculated to deliver 2 to 6 mg per minute, depending on body weight, renal elimination rate, and steady-state plasma level needed to maintain control of the arrhythmia*. The 4 mg/mL maintenance concentration may be preferred if total infused volume must be limited.

†(All infusions should be made up to final volume with 5% Dextrose Injection, USP.)
*Please see text under DOSAGE AND ADMINISTRATION for further details. The flow rate of any intravenous procainamide infusion must be monitored closely to avoid transiently high plasma levels and possible hypotension (see PRECAUTIONS).

Parenteral drug products should be examined visually for particulate matter and discoloration (see HOW SUPPLIED) prior to administration.

HOW SUPPLIED

Procainamide Hydrochloride Injection, USP is available in multiple-dose 10 mL vials providing 100 mg procainamide hydrochloride per mL.

Unit of Sale | Concentration
NDC 0409-1902-01 Case containing 25 cartons of 1 multiple-dose vial | 1 g/10 mL (100 mg/mL)

The solutions, which are clear and colorless initially, may develop a slightly yellow color in time. This does not indicate a change which should preclude its use, but a solution any darker than light amber or otherwise discolored should not be used.

Store at 20°C to 25°C (68°F to 77°F). [See USP Controlled Room Temperature.]

Distributed by Hospira Inc., Lake Forest, IL 60045 USA

LAB-1321-4.0

Revised: 02/2026

PRINCIPAL DISPLAY PANEL - 10 mL Vial Label

10 mL Multiple-dose
PROCAINAMIDE
HCl Injection, USP

1 gram/10 mL TOTAL
(100 mg/mL)

Dist. by Hospira, Inc., Lake Forest, IL 60045 USA

PRINCIPAL DISPLAY PANEL - 10 mL Vial Carton

One/NDC 0409-1902-11
Rx only

10 mL
Multiple-dose

PROCAINAMIDE
HYDROCHLORIDE
Injection, USP

1 gram/10 mL TOTAL
(100 mg/mL)

Warning: Contains Metabisulfites